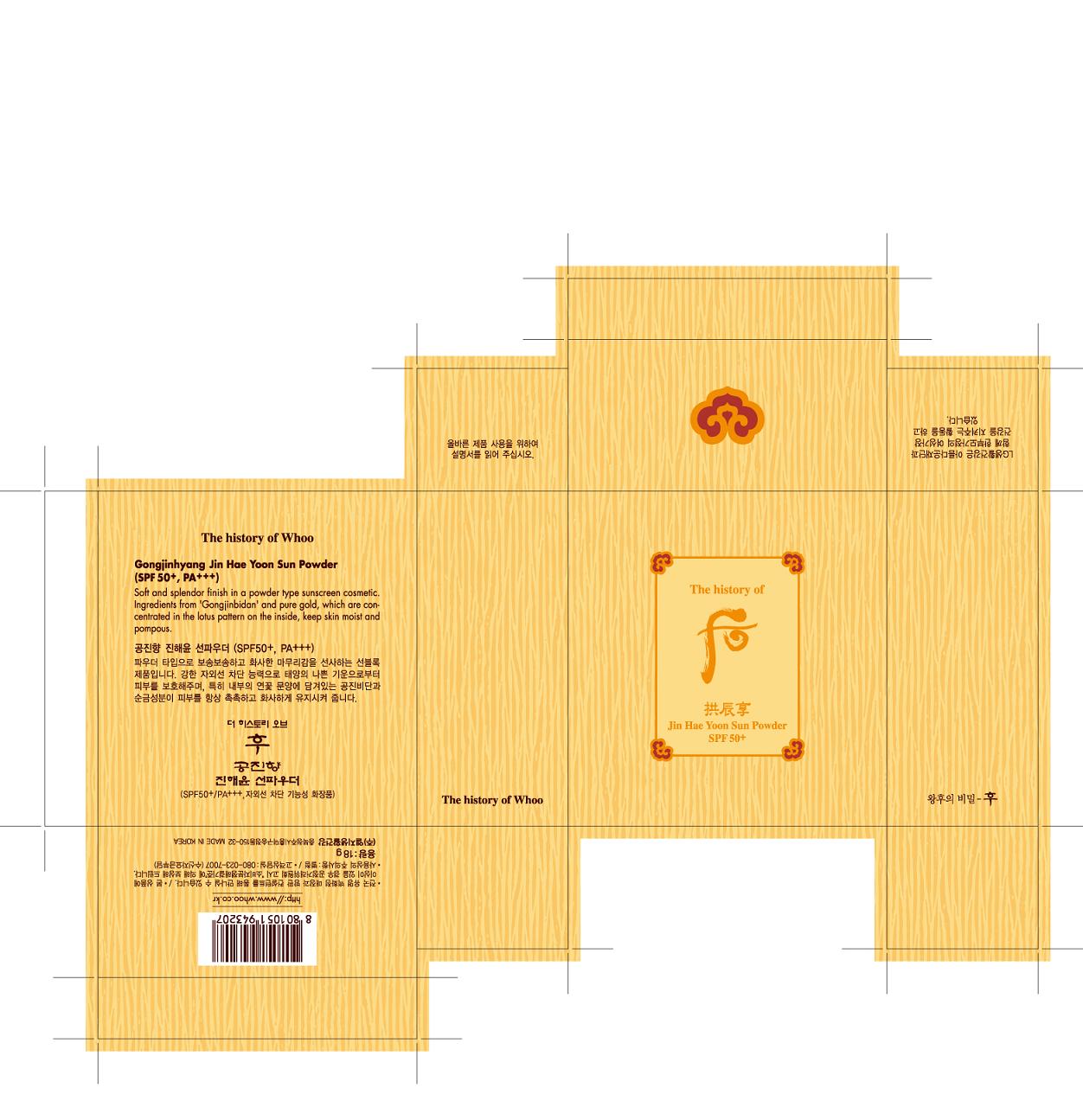 DRUG LABEL: Whoo Gong Jin Hyang Jin Hae Yoon Sun
NDC: 53208-513 | Form: POWDER
Manufacturer: LG Household and Healthcare, Inc.
Category: otc | Type: HUMAN OTC DRUG LABEL
Date: 20110329

ACTIVE INGREDIENTS: OCTINOXATE 7.2 g/100 g; ZINC OXIDE 4.8 g/100 g; TITANIUM DIOXIDE 2.125 g/100 g; BISOCTRIZOLE 2.125 g/100 g
INACTIVE INGREDIENTS: TALC; SILICON DIOXIDE; ALUMINUM HYDROXIDE; DIMETHICONE; MICA; METHYLPARABEN; LAUROYL LYSINE; PROPYLPARABEN; STEARIC ACID; GOLD; BORON NITRIDE; ALUMINUM STARCH OCTENYLSUCCINATE; 1,2-HEXANEDIOL; MAGNESIUM MYRISTATE; MAGNESIUM; Ceramide 3; POLYSORBATE 60; SORBITAN MONOSTEARATE; SORBITAN; DIOSCOREA JAPONICA ROOT

DRUG FACTS

ACTIVE INGREDIENT

BISOCTRIZOLE 2.125%
OCTINOXATE 7.2%
ZINC OXIDE 4.8%
TITANIUM DIOXIDE 2.15%

WARNINGS AND PRECAUTIONS

For external use only

Keep out of reach of children. Is swallowed, get medical help or contact a Poison Control Center right away.

WHEN USING

Keep out of eyes. Rinse with water to remove.

Stop use if a rash or irritation develops and lasts.

PACKAGE LABEL

Whoo

Jin Hae Yoon Powder